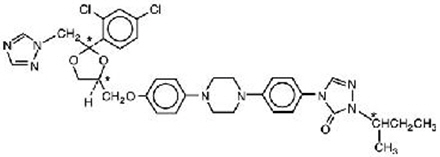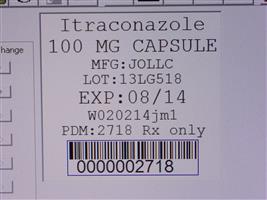 DRUG LABEL: itraconazole
NDC: 68151-2718 | Form: CAPSULE
Manufacturer: Carilion Materials Management
Category: prescription | Type: HUMAN PRESCRIPTION DRUG LABEL
Date: 20160804

ACTIVE INGREDIENTS: ITRACONAZOLE 100 mg/1 1
INACTIVE INGREDIENTS: GELATIN; HYPROMELLOSES; POLYETHYLENE GLYCOLS; starch, corn; SUCROSE; TITANIUM DIOXIDE; FD&C Blue No. 1; FD&C Blue No. 2; D&C Red No. 22; D&C Red No. 28

Itraconazole Capsules

PATRIOT
Pharmaceuticals

Itraconazole
Capsules

BOXED WARNING

Congestive Heart Failure, Cardiac Effects and Drug Interactions

Itraconazole Capsules should not be administered for the treatment of onychomycosis in patients with evidence of ventricular dysfunction such as congestive heart failure (CHF) or a history of CHF. If signs or symptoms of congestive heart failure occur during administration of Itraconazole Capsules, discontinue administration. When itraconazole was administered intravenously to dogs and healthy human volunteers, negative inotropic effects were seen. (See CONTRAINDICATIONS, WARNINGS, PRECAUTIONS: Drug Interactions, ADVERSE REACTIONS: Post-marketing Experience, and CLINICAL PHARMACOLOGY: Special Populations for more information.)

Drug Interactions

Coadministration of the following drugs are contraindicated with Itraconazole Capsules: methadone, disopyramide, dofetilide, dronedarone, quinidine, ergot alkaloids (such as dihydroergotamine, ergometrine (ergonovine), ergotamine, methylergometrine (methylergonovine)), irinotecan, lurasidone, oral midazolam, pimozide, triazolam, felodipine, nisoldipine, ranolazine, eplerenone, cisapride, lovastatin, simvastatin, ticagrelor and, in subjects with varying degrees of renal or hepatic impairment, colchicine, fesoterodine, telithromycin and solifenacin. See PRECAUTIONS: Drug Interactions Section for specific examples. Coadministration with itraconazole can cause elevated plasma concentrations of these drugs and may increase or prolong both the pharmacologic effects and/or adverse reactions to these drugs. For example, increased plasma concentrations of some of these drugs can lead to QT prolongation and ventricular tachyarrhythmias including occurrences of torsades de pointes, a potentially fatal arrhythmia. See CONTRAINDICATIONS and WARNINGS Sections, and PRECAUTIONS: Drug Interactions Section for specific examples.

DESCRIPTION

Itraconazole is an azole antifungal agent. Itraconazole is a 1:1:1:1 racemic mixture of four diastereomers (two enantiomeric pairs), each possessing three chiral centers. It may be represented by the following structural formula and nomenclature:

(±)-1-[(R*)-sec-butyl]-4-[p-[4-[p-[[(2R*,4S*)-2-(2,4-dichlorophenyl)-2-(1H-1,2,4-triazol-1-ylmethyl)-1,3-dioxolan-4-yl]methoxy]phenyl]-1-piperazinyl]phenyl]-Δ^2-1,2,4-triazolin-5-one mixture with (±)-1-[(R*)-sec-butyl]-4-[p-[4-[p-[[(2S*,4R*)-2-(2,4-dichlorophenyl)-2-(1H-1,2,4-triazol-1-ylmethyl)-1,3-dioxolan-4-yl]methoxy]phenyl]-1-piperazinyl]phenyl]-Δ^2-1,2,4-triazolin-5-one

or

(±)-1-[(RS)-sec-butyl]-4-[p-[4-[p-[[(2R,4S)-2-(2,4-dichlorophenyl)-2-(1H-1,2,4-triazol-1-ylmethyl)-1,3-dioxolan-4-yl]methoxy]phenyl]-1-piperazinyl]phenyl]-Δ^2-1,2,4-triazolin-5-one

Itraconazole has a molecular formula of C35H38Cl2N8O4 and a molecular weight of 705.64. It is a white to slightly yellowish powder. It is insoluble in water, very slightly soluble in alcohols, and freely soluble in dichloromethane. It has a pKa of 3.70 (based on extrapolation of values obtained from methanolic solutions) and a log (n-octanol/water) partition coefficient of 5.66 at pH 8.1.

Itraconazole Capsules contain 100 mg of itraconazole coated on sugar spheres (composed of sucrose, maize starch, and purified water). Inactive ingredients are hard gelatin capsule, hypromellose, polyethylene glycol (PEG) 20,000, titanium dioxide, FD&C Blue No. 1, FD&C Blue No. 2, D&C Red No. 22 and D&C Red No. 28.

CLINICAL PHARMACOLOGY

Pharmacokinetics and Metabolism

General Pharmacokinetic Characteristics

Peak plasma concentrations of itraconazole are reached within 2 to 5 hours following oral administration. As a consequence of non-linear pharmacokinetics, itraconazole accumulates in plasma during multiple dosing. Steady-state concentrations are generally reached within about 15 days, with Cmax values of 0.5 µg/mL, 1.1 µg/mL and 2.0 µg/mL after oral administration of 100 mg once daily, 200 mg once daily and 200 mg b.i.d., respectively. The terminal half-life of itraconazole generally ranges from 16 to 28 hours after single dose and increases to 34 to 42 hours with repeated dosing. Once treatment is stopped, itraconazole plasma concentrations decrease to an almost undetectable concentration within 7 to 14 days, depending on the dose and duration of treatment. Itraconazole mean total plasma clearance following intravenous administration is 278 mL/min. Itraconazole clearance decreases at higher doses due to saturable hepatic metabolism.

Absorption

Itraconazole is rapidly absorbed after oral administration. Peak plasma concentrations of itraconazole are reached within 2 to 5 hours following an oral capsule dose. The observed absolute oral bioavailability of itraconazole is about 55%.

The oral bioavailability of itraconazole is maximal when Itraconazole Capsules are taken immediately after a full meal.

Absorption of itraconazole capsules is reduced in subjects with reduced gastric acidity, such as subjects taking medications known as gastric acid secretion suppressors (e.g., H2-receptor antagonists, proton pump inhibitors) or subjects with achlorhydria caused by certain diseases. (See PRECAUTIONS: Drug Interactions.) Absorption of itraconazole under fasted conditions in these subjects is increased when Itraconazole Capsules are administered with an acidic beverage (such as a non-diet cola). When Itraconazole Capsules were administered as a single 200-mg dose under fasted conditions with non-diet cola after ranitidine pretreatment, a H2-receptor antagonist, itraconazole absorption was comparable to that observed when Itraconazole Capsules were administered alone. (See PRECAUTIONS: Drug Interactions.)

Itraconazole exposure is lower with the Capsule formulation than with the Oral Solution when the same dose of drug is given. (See WARNINGS)

Distribution

Most of the itraconazole in plasma is bound to protein (99.8%), with albumin being the main binding component (99.6% for the hydroxy-metabolite). It has also a marked affinity for lipids. Only 0.2% of the itraconazole in plasma is present as free drug. Itraconazole is distributed in a large apparent volume in the body (>700 L), suggesting extensive distribution into tissues. Concentrations in lung, kidney, liver, bone, stomach, spleen and muscle were found to be two to three times higher than corresponding concentrations in plasma, and the uptake into keratinous tissues, skin in particular, up to four times higher. Concentrations in the cerebrospinal fluid are much lower than in plasma.

Metabolism

Itraconazole is extensively metabolized by the liver into a large number of metabolites. In vitro studies have shown that CYP3A4 is the major enzyme involved in the metabolism of itraconazole. The main metabolite is hydroxy-itraconazole, which has in vitro antifungal activity comparable to itraconazole; trough plasma concentrations of this metabolite are about twice those of itraconazole.

Excretion

Itraconazole is excreted mainly as inactive metabolites in urine (35%) and in feces (54%) within one week of an oral solution dose. Renal excretion of itraconazole and the active metabolite hydroxy-itraconazole account for less than 1% of an intravenous dose. Based on an oral radiolabeled dose, fecal excretion of unchanged drug ranges from 3% to 18% of the dose.

As re-distribution of itraconazole from keratinous tissues appears to be negligible, elimination of itraconazole from these tissues is related to epidermal regeneration. Contrary to plasma, the concentration in skin persists for 2 to 4 weeks after discontinuation of a 4-week treatment and in nail keratin – where itraconazole can be detected as early as 1 week after start of treatment – for at least six months after the end of a 3-month treatment period.

Special Populations

Renal Impairment

Limited data are available on the use of oral itraconazole in patients with renal impairment. A pharmacokinetic study using a single 200-mg oral dose of itraconazole was conducted in three groups of patients with renal impairment (uremia: n=7; hemodialysis: n=7; and continuous ambulatory peritoneal dialysis: n=5). In uremic subjects with a mean creatinine clearance of 13 mL/min. × 1.73 m^2, the exposure, based on AUC, was slightly reduced compared with normal population parameters. This study did not demonstrate any significant effect of hemodialysis or continuous ambulatory peritoneal dialysis on the pharmacokinetics of itraconazole (Tmax, Cmax, and AUC0–8h). Plasma concentration-versus-time profiles showed wide intersubject variation in all three groups. After a single intravenous dose, the mean terminal half-lives of itraconazole in patients with mild (defined in this study as CrCl 50–79 mL/min), moderate (defined in this study as CrCl 20–49 mL/min), and severe renal impairment (defined in this study as CrCl <20 mL/min) were similar to that in healthy subjects (range of means 42–49 hours vs 48 hours in renally impaired patients and healthy subjects, respectively). Overall exposure to itraconazole, based on AUC, was decreased in patients with moderate and severe renal impairment by approximately 30% and 40%, respectively, as compared with subjects with normal renal function. Data are not available in renally impaired patients during long-term use of itraconazole. Dialysis has no effect on the half-life or clearance of itraconazole or hydroxy-itraconazole. (See PRECAUTIONS and DOSAGE AND ADMINISTRATION.)

Hepatic Impairment

Itraconazole is predominantly metabolized in the liver. A pharmacokinetic study was conducted in 6 healthy and 12 cirrhotic subjects who were administered a single 100-mg dose of itraconazole as capsule. A statistically significant reduction in mean Cmax (47%) and a twofold increase in the elimination half-life (37 ± 17 hours vs. 16 ± 5 hours) of itraconazole were noted in cirrhotic subjects compared with healthy subjects. However, overall exposure to itraconazole, based on AUC, was similar in cirrhotic patients and in healthy subjects. Data are not available in cirrhotic patients during long-term use of itraconazole. (See CONTRAINDICATIONS, PRECAUTIONS: Drug Interactions and DOSAGE AND ADMINISTRATION.)

Decreased Cardiac Contractility

When itraconazole was administered intravenously to anesthetized dogs, a dose-related negative inotropic effect was documented. In a healthy volunteer study of itraconazole intravenous infusion, transient, asymptomatic decreases in left ventricular ejection fraction were observed using gated SPECT imaging; these resolved before the next infusion, 12 hours later. If signs or symptoms of congestive heart failure appear during administration of Itraconazole Capsules, itraconazole should be discontinued. (See BOXED WARNING, CONTRAINDICATIONS, WARNINGS, PRECAUTIONS: Drug Interactions and ADVERSE REACTIONS: Post-marketing Experience for more information.)

MICROBIOLOGY

Mechanism of Action

In vitro studies have demonstrated that itraconazole inhibits the cytochrome P450-dependent synthesis of ergosterol, which is a vital component of fungal cell membranes.

Activity In Vitro and in Clinical Infections

Itraconazole exhibits in vitro activity against Blastomyces dermatitidis, Histoplasma capsulatum, Histoplasma duboisii, Aspergillus flavus, Aspergillus fumigatus, and Trichophyton species (See INDICATIONS AND USAGE, Description of Clinical Studies).

Correlation between minimum inhibitory concentration (MIC) results in vitro and clinical outcome has yet to be established for azole antifungal agents.

Drug Resistance

Isolates from several fungal species with decreased susceptibility to itraconazole have been isolated in vitro and from patients receiving prolonged therapy.

Itraconazole is not active against Zygomycetes (e.g., Rhizopus spp., Rhizomucor spp., Mucor spp. and Absidia spp.), Fusarium spp., Scedosporium spp. and Scopulariopsis spp.

Cross-resistance

Several in vitro studies have reported that some fungal clinical isolates with reduced susceptibility to one azole antifungal agent may also be less susceptible to other azole derivatives. The finding of cross-resistance is dependent on a number of factors, including the species evaluated, its clinical history, the particular azole compounds compared, and the type of susceptibility test that is performed.

Studies (both in vitro and in vivo) suggest that the activity of amphotericin B may be suppressed by prior azole antifungal therapy. As with other azoles, itraconazole inhibits the ^14C-demethylation step in the synthesis of ergosterol, a cell wall component of fungi. Ergosterol is the active site for amphotericin B. In one study the antifungal activity of amphotericin B against Aspergillus fumigatus infections in mice was inhibited by ketoconazole therapy. The clinical significance of test results obtained in this study is unknown.

INDICATIONS AND USAGE

Itraconazole Capsules are indicated for the treatment of the following fungal infections in immunocompromised and non-immunocompromised patients:

1. Blastomycosis, pulmonary and extrapulmonary
2. Histoplasmosis, including chronic cavitary pulmonary disease and disseminated, non-meningeal histoplasmosis, and
3. Aspergillosis, pulmonary and extrapulmonary, in patients who are intolerant of or who are refractory to amphotericin B therapy.

Specimens for fungal cultures and other relevant laboratory studies (wet mount, histopathology, serology) should be obtained before therapy to isolate and identify causative organisms. Therapy may be instituted before the results of the cultures and other laboratory studies are known; however, once these results become available, antiinfective therapy should be adjusted accordingly.

Itraconazole Capsules are also indicated for the treatment of the following fungal infections in non-immunocompromised patients:

1. Onychomycosis of the toenail, with or without fingernail involvement, due to dermatophytes (tinea unguium), and
2. Onychomycosis of the fingernail due to dermatophytes (tinea unguium).

Prior to initiating treatment, appropriate nail specimens for laboratory testing (KOH preparation, fungal culture, or nail biopsy) should be obtained to confirm the diagnosis of onychomycosis.

(See CLINICAL PHARMACOLOGY: Special Populations, CONTRAINDICATIONS, WARNINGS, and ADVERSE REACTIONS: Post-marketing Experience for more information.)

Description of Clinical Studies

Blastomycosis

Analyses were conducted on data from two open-label, non-concurrently controlled studies (N=73 combined) in patients with normal or abnormal immune status. The median dose was 200 mg/day. A response for most signs and symptoms was observed within the first 2 weeks, and all signs and symptoms cleared between 3 and 6 months. Results of these two studies demonstrated substantial evidence of the effectiveness of itraconazole for the treatment of blastomycosis compared with the natural history of untreated cases.

Histoplasmosis

Analyses were conducted on data from two open-label, non-concurrently controlled studies (N=34 combined) in patients with normal or abnormal immune status (not including HIV-infected patients). The median dose was 200 mg/day. A response for most signs and symptoms was observed within the first 2 weeks, and all signs and symptoms cleared between 3 and 12 months. Results of these two studies demonstrated substantial evidence of the effectiveness of itraconazole for the treatment of histoplasmosis, compared with the natural history of untreated cases.

Histoplasmosis in HIV-infected patients

Data from a small number of HIV-infected patients suggested that the response rate of histoplasmosis in HIV-infected patients is similar to that of non-HIV-infected patients. The clinical course of histoplasmosis in HIV-infected patients is more severe and usually requires maintenance therapy to prevent relapse.

Aspergillosis

Analyses were conducted on data from an open-label, "single-patient-use" protocol designed to make itraconazole available in the U.S. for patients who either failed or were intolerant of amphotericin B therapy (N=190). The findings were corroborated by two smaller open-label studies (N=31 combined) in the same patient population. Most adult patients were treated with a daily dose of 200 to 400 mg, with a median duration of 3 months. Results of these studies demonstrated substantial evidence of effectiveness of itraconazole as a second-line therapy for the treatment of aspergillosis compared with the natural history of the disease in patients who either failed or were intolerant of amphotericin B therapy.

Onychomycosis of the toenail

Analyses were conducted on data from three double-blind, placebo-controlled studies (N=214 total; 110 given Itraconazole Capsules) in which patients with onychomycosis of the toenails received 200 mg of Itraconazole Capsules once daily for 12 consecutive weeks. Results of these studies demonstrated mycologic cure, defined as simultaneous occurrence of negative KOH plus negative culture, in 54% of patients. Thirty-five percent (35%) of patients were considered an overall success (mycologic cure plus clear or minimal nail involvement with significantly decreased signs) and 14% of patients demonstrated mycologic cure plus clinical cure (clearance of all signs, with or without residual nail deformity). The mean time to overall success was approximately 10 months. Twenty-one percent (21%) of the overall success group had a relapse (worsening of the global score or conversion of KOH or culture from negative to positive).

Onychomycosis of the fingernail

Analyses were conducted on data from a double-blind, placebo-controlled study (N=73 total; 37 given Itraconazole Capsules) in which patients with onychomycosis of the fingernails received a 1-week course (pulse) of 200 mg of Itraconazole Capsules b.i.d., followed by a 3-week period without Itraconazole Capsules, which was followed by a second 1-week pulse of 200 mg of Itraconazole Capsules b.i.d. Results demonstrated mycologic cure in 61% of patients. Fifty-six percent (56%) of patients were considered an overall success and 47% of patients demonstrated mycologic cure plus clinical cure. The mean time to overall success was approximately 5 months. None of the patients who achieved overall success relapsed.

CONTRAINDICATIONS

Congestive Heart Failure

Itraconazole Capsules should not be administered for the treatment of onychomycosis in patients with evidence of ventricular dysfunction such as congestive heart failure (CHF) or a history of CHF. (See BOXED WARNING, WARNINGS, PRECAUTIONS: Drug Interactions-Calcium Channel Blockers, ADVERSE REACTIONS: Post-marketing Experience, and CLINICAL PHARMACOLOGY: Special Populations.)

Drug Interactions

Coadministration of a number of CYP3A4 substrates are contraindicated with itraconazole. Plasma concentrations increase for the following drugs: methadone, disopyramide, dofetilide, dronedarone, quinidine, ergot alkaloids (such as dihydroergotamine, ergometrine (ergonovine), ergotamine, methylergometrine (methylergonovine)), irinotecan, lurasidone, oral midazolam, pimozide, triazolam, felodipine, nisoldipine, ranolazine, eplerenone, cisapride, lovastatin, simvastatin, ticagrelor, and, in subjects with varying degrees of renal or hepatic impairment, colchicine, fesoterodine, telithromycin and solifenacin. (See PRECAUTIONS: Drug Interactions Section for specific examples.) This increase in drug concentrations caused by coadministration with itraconazole, may increase or prolong both the pharmacologic effect and/or adverse reactions to these drugs. For example, increased plasma concentrations of some of these drugs can lead to QT prolongation and ventricular tachyarrhythmias including occurrences of torsade de pointes, a potentially fatal arrhythmia. Specific examples are listed in PRECAUTIONS: Drug Interactions.

Itraconazole should not be administered for the treatment of onychomycosis to pregnant patients or to women contemplating pregnancy.

Itraconazole is contraindicated for patients who have shown hypersensitivity to itraconazole. There is limited information regarding cross-hypersensitivity between itraconazole and other azole antifungal agents. Caution should be used when prescribing itraconazole to patients with hypersensitivity to other azoles.

WARNINGS

Hepatic Effects

Itraconazole has been associated with rare cases of serious hepatotoxicity, including liver failure and death. Some of these cases had neither pre-existing liver disease nor a serious underlying medical condition, and some of these cases developed within the first week of treatment. If clinical signs or symptoms develop that are consistent with liver disease, treatment should be discontinued and liver function testing performed. Continued itraconazole use or reinstitution of treatment with itraconazole is strongly discouraged unless there is a serious or life-threatening situation where the expected benefit exceeds the risk. (See PRECAUTIONS: Information for Patients and ADVERSE REACTIONS.)

Cardiac Dysrhythmias

Life-threatening cardiac dysrhythmias and/or sudden death have occurred in patients using drugs such as cisapride, pimozide, methadone, or quinidine concomitantly with itraconazole and/or other CYP3A4 inhibitors. Concomitant administration of these drugs with itraconazole is contraindicated. (See BOXED WARNING, CONTRAINDICATIONS, and PRECAUTIONS: Drug Interactions.)

Cardiac Disease

Itraconazole Capsules should not be administered for the treatment of onychomycosis in patients with evidence of ventricular dysfunction such as congestive heart failure (CHF) or a history of CHF. Itraconazole Capsules should not be used for other indications in patients with evidence of ventricular dysfunction unless the benefit clearly outweighs the risk.

For patients with risk factors for congestive heart failure, physicians should carefully review the risks and benefits of itraconazole therapy. These risk factors include cardiac disease such as ischemic and valvular disease; significant pulmonary disease such as chronic obstructive pulmonary disease; and renal failure and other edematous disorders. Such patients should be informed of the signs and symptoms of CHF, should be treated with caution, and should be monitored for signs and symptoms of CHF during treatment. If signs or symptoms of CHF appear during administration of Itraconazole Capsules, discontinue administration.

Itraconazole has been shown to have a negative inotropic effect. When itraconazole was administered intravenously to anesthetized dogs, a dose-related negative inotropic effect was documented. In a healthy volunteer study of itraconazole intravenous infusion, transient, asymptomatic decreases in left ventricular ejection fraction were observed using gated SPECT imaging; these resolved before the next infusion, 12 hours later.

Itraconazole has been associated with reports of congestive heart failure. In post-marketing experience, heart failure was more frequently reported in patients receiving a total daily dose of 400 mg although there were also cases reported among those receiving lower total daily doses.

Calcium channel blockers can have negative inotropic effects which may be additive to those of itraconazole. In addition, itraconazole can inhibit the metabolism of calcium channel blockers. Therefore, caution should be used when co-administering itraconazole and calcium channel blockers due to an increased risk of CHF. Concomitant administration of itraconazole and felodipine or nisoldipine is contraindicated.

Cases of CHF, peripheral edema, and pulmonary edema have been reported in the post-marketing period among patients being treated for onychomycosis and/or systemic fungal infections. (See CLINICAL PHARMACOLOGY: Special Populations, CONTRAINDICATIONS, PRECAUTIONS: Drug Interactions, and ADVERSE REACTIONS: Post-marketing Experience for more information.)

Interaction potential

Itraconazole has a potential for clinically important drug interactions. Coadministration of specific drugs with itraconazole may result in changes in efficacy of itraconazole and/or the coadministered drug, life-threatening effects and/or sudden death. Drugs that are contraindicated, not recommended or recommended for use with caution in combination with itraconazole are listed in PRECAUTIONS: Drug Interactions.

Interchangeability

Itraconazole Capsules and SPORANOX® (itraconazole) Oral Solution should not be used interchangeably. This is because drug exposure is greater with the Oral Solution than with the Capsules when the same dose of drug is given. In addition, the topical effects of mucosal exposure may be different between the two formulations. Only the Oral Solution has been demonstrated effective for oral and/or esophageal candidiasis.

PRECAUTIONS

General

Itraconazole Capsules should be administered after a full meal. (See CLINICAL PHARMACOLOGY: Pharmacokinetics and Metabolism).

Under fasted conditions, itraconazole absorption was decreased in the presence of decreased gastric acidity. The absorption of itraconazole may be decreased with the concomitant administration of antacids or gastric acid secretion suppressors. Studies conducted under fasted conditions demonstrated that administration with 8 ounces of a non-diet cola beverage resulted in increased absorption of itraconazole in AIDS patients with relative or absolute achlorhydria. This increase relative to the effects of a full meal is unknown. (See CLINICAL PHARMACOLOGY: Pharmacokinetics and Metabolism).

Hepatotoxicity

Rare cases of serious hepatotoxicity have been observed with itraconazole treatment, including some cases within the first week. It is recommended that liver function monitoring be considered in all patients receiving itraconazole. Treatment should be stopped immediately and liver function testing should be conducted in patients who develop signs and symptoms suggestive of liver dysfunction.

Neuropathy

If neuropathy occurs that may be attributable to Itraconazole Capsules, the treatment should be discontinued.

Cystic Fibrosis

If a cystic fibrosis patient does not respond to Itraconazole Capsules, consideration should be given to switching to alternative therapy. For more information concerning the use of itraconazole in cystic fibrosis patients see the prescribing information for SPORANOX® Oral Solution.

Hearing Loss

Transient or permanent hearing loss has been reported in patients receiving treatment with itraconazole. Several of these reports included concurrent administration of quinidine which is contraindicated (see BOXED WARNING: Drug Interactions, CONTRAINDICATIONS: Drug Interactions and PRECAUTIONS: Drug Interactions). The hearing loss usually resolves when treatment is stopped, but can persist in some patients.

Information for Patients

- The topical effects of mucosal exposure may be different between Itraconazole Capsules and SPORANOX® (itraconazole) Oral Solution. Only the Oral Solution has been demonstrated effective for oral and/or esophageal candidiasis. Itraconazole Capsules should not be used interchangeably with SPORANOX® Oral Solution.
- Instruct patients to take Itraconazole Capsules with a full meal. Itraconazole Capsules must be swallowed whole.
- Instruct patients about the signs and symptoms of congestive heart failure, and if these signs or symptoms occur during itraconazole administration, they should discontinue itraconazole and contact their healthcare provider immediately.
- Instruct patients to stop itraconazole treatment immediately and contact their healthcare provider if any signs and symptoms suggestive of liver dysfunction develop. Such signs and symptoms may include unusual fatigue, anorexia, nausea and/or vomiting, jaundice, dark urine, or pale stools.
- Instruct patients to contact their physician before taking any concomitant medications with itraconazole to ensure there are no potential drug interactions.
- Instruct patients that hearing loss can occur with the use of itraconazole. The hearing loss usually resolves when treatment is stopped, but can persist in some patients. Advise patients to discontinue therapy and inform their physicians if any hearing loss symptoms occur.
- Instruct patients that dizziness or blurred/double vision can sometimes occur with itraconazole. Advise patients that if they experience these events, they should not drive or use machines.

Drug Interactions

Itraconazole is mainly metabolized through CYP3A4. Other drugs that either share this metabolic pathway or modify CYP3A4 activity may influence the pharmacokinetics of itraconazole. Similarly, itraconazole may modify the pharmacokinetics of other drugs that share this metabolic pathway. Itraconazole is a potent CYP3A4 inhibitor and a P-glycoprotein inhibitor. When using concomitant medication, it is recommended that the corresponding label be consulted for information on the route of metabolism and the possible need to adjust dosages.

Drugs that may decrease itraconazole plasma concentrations

Drugs that reduce the gastric acidity (e.g. acid neutralizing medicines such as aluminum hydroxide, or acid secretion suppressors such as H2-receptor antagonists and proton pump inhibitors) impair the absorption of itraconazole from Itraconazole Capsules. It is recommended that these drugs be used with caution when coadministered with Itraconazole Capsules:

- It is recommended that itraconazole capsules be administered with an acidic beverage (such as non-diet cola) upon co-treatment with drugs reducing gastric acidity.
- It is recommended that acid neutralizing medicines (e.g. aluminum hydroxide) be administered at least 1 hour before or 2 hours after the intake of Itraconazole Capsules.
- Upon coadministration, it is recommended that the antifungal activity be monitored and the itraconazole dose increased as deemed necessary.

Coadministration of itraconazole with potent enzyme inducers of CYP3A4 may decrease the bioavailability of itraconazole and hydroxy-itraconazole to such an extent that efficacy may be reduced. Examples include:

- Antibacterials: isoniazid, rifabutin (see also under 'Drugs that may have their plasma concentrations increased by itraconazole'), rifampicin
- Anticonvulsants: carbamazepine, (see also under 'Drugs that may have their plasma concentrations increased by itraconazole'), phenobarbital, phenytoin
- Antivirals: efavirenz, nevirapine

Therefore, administration of potent enzyme inducers of CYP3A4 with itraconazole is not recommended. It is recommended that the use of these drugs be avoided from 2 weeks before and during treatment with itraconazole, unless the benefits outweigh the risk of potentially reduced itraconazole efficacy. Upon coadministration, it is recommended that the antifungal activity be monitored and the itraconazole dose increased as deemed necessary.

Drugs that may increase itraconazole plasma concentrations

Potent inhibitors of CYP3A4 may increase the bioavailability of itraconazole. Examples include:

- Antibacterials: ciprofloxacin, clarithromycin, erythromycin
- Antivirals: ritonavir-boosted darunavir, ritonavir-boosted fosamprenavir, indinavir (see also under 'Drugs that may have their plasma concentrations increased by itraconazole'), ritonavir (see also under 'Drugs that may have their plasma concentrations increased by itraconazole') and telaprevir.

It is recommended that these drugs be used with caution when coadministered with Itraconazole Capsules. It is recommended that patients who must take itraconazole concomitantly with potent inhibitors of CYP3A4 be monitored closely for signs or symptoms of increased or prolonged pharmacologic effects of itraconazole, and the itraconazole dose be decreased as deemed necessary.

Drugs that may have their plasma concentrations increased by itraconazole

Itraconazole and its major metabolite, hydroxy-itraconazole, can inhibit the metabolism of drugs metabolized by CYP3A4 and can inhibit the drug transport by P-glycoprotein, which may result in increased plasma concentrations of these drugs and/or their active metabolite(s) when they are administered with itraconazole. These elevated plasma concentrations may increase or prolong both therapeutic and adverse effects of these drugs. CYP3A4-metabolized drugs known to prolong the QT interval may be contraindicated with itraconazole, since the combination may lead to ventricular tachyarrhythmias including occurrences of torsade de pointes, a potentially fatal arrhythmia. Once treatment is stopped, itraconazole plasma concentrations decrease to an almost undetectable concentration within 7 to 14 days, depending on the dose and duration of treatment. In patients with hepatic cirrhosis or in subjects receiving CYP3A4 inhibitors, the decline in plasma concentrations may be even more gradual. This is particularly important when initiating therapy with drugs whose metabolism is affected by itraconazole.

Examples of drugs that may have their plasma concentrations increased by itraconazole presented by drug class with advice regarding coadministration with itraconazole:

Table 1: Drugs that may have their plasma concentrations increased by itraconazole
Drug Class | Contraindicated | Not Recommended | Use with Caution | Comments
 | Under no circumstances is the drug to be coadministered with itraconazole, and up to two weeks after discontinuation of treatment with itraconazole. | It is recommended that the use of the drug be avoided during and up to two weeks after discontinuation of treatment with itraconazole, unless the benefits outweigh the potentially increased risks of side effects. If coadministration cannot be avoided, clinical monitoring for signs or symptoms of increased or prolonged effects or side effects of the interacting drug is recommended, and its dosage be reduced or interrupted as deemed necessary. When appropriate, it is recommended that plasma concentrations be measured. The label of the coadministered drug should be consulted for information on dose adjustment and adverse effects. | Careful monitoring is recommended when the drug is coadministered with itraconazole. Upon coadministration, it is recommended that patients be monitored closely for signs or symptoms of increased or prolonged effects or side effects of the interacting drug, and its dosage be reduced as deemed necessary. When appropriate, it is recommended that plasma concentrations be measured. The label of the coadministered drug should be consulted for information on dose adjustment and adverse effects.
Alpha Blockers |  | tamsulosin
Analgesics | methadone |  | alfentanil, buprenorphine IV and sublingual, fentanyl, oxycodone, sufentanil | Methadone: The potential increase in plasma concentrations of methadone when coadministered with itraconazole may increase the risk of serious cardiovascular events including QTc prolongation and torsade de pointes.
 |  |  |  | Fentanyl: The potential increase in plasma concentrations of fentanyl when coadministered with itraconazole may increase the risk of potentially fatal respiratory depression.
 |  |  |  | Sufentanil: No human pharmacokinetic data of an interaction with itraconazole are available. In vitro data suggest that sufentanil is metabolized by CYP3A4 and so potentially increased sufentanil plasma concentrations would be expected when coadministered with itraconazole.
Antiarrhythmics | disopyramide, dofetilide, dronedarone, quinidine |  | digoxin | Disopyramide, dofetilide, dronedarone, quinidine: The potential increase in plasma concentrations of these drugs when coadministered with itraconazole may increase the risk of serious cardiovascular events including QTc prolongation.
Antibacterials | telithromycin, in subjects with severe renal impairment or severe hepatic impairment | rifabutin | telithromycin | Telithromycin: The potential increase in plasma concentrations of telithromycin in subjects with severe renal impairment or severe hepatic impairment, when coadministered with Itraconazole Capsules may increase the risk of serious cardiovascular events including QT prolongation and torsade de pointes. Rifabutin: See also under 'Drugs that may decrease itraconazole plasma concentrations'.
Anticoagulants and Antiplatelet Drugs | ticagrelor | apixaban, rivaroxaban | coumarins, cilostazol, dabigatran | Ticagrelor: The potential increase in plasma concentrations of ticagrelor may increase the risk of bleeding. Coumarins: Itraconazole may enhance the anticoagulant effect of coumarin-like drugs, such as warfarin.
Anticonvulsants |  | carbamazepine |  | Carbamazepine: In vivo studies have demonstrated an increase in plasma carbamazepine concentrations in subjects concomitantly receiving ketoconazole. Although there are no data regarding the effect of itraconazole on carbamazepine metabolism, because of the similarities between ketoconazole and itraconazole, concomitant administration of itraconazole and carbamazepine may inhibit the metabolism of carbamazepine. See also under 'Drugs that may decrease itraconazole plasma concentrations'.
Antidiabetics |  |  | repaglinide, saxagliptin
Antihelmintics and Antiprotozoals |  |  | praziquantel
Antimigraine Drugs | ergot alkaloids, such as dihydroergotamine, ergometrine (ergonovine), ergotamine, methylergometrine (methylergonovine) |  | eletriptan | Ergot Alkaloids: The potential increase in plasma concentrations of ergot alkaloids when coadministered with itraconazole may increase the risk of ergotism, ie. a risk for vasospasm potentially leading to cerebral ischemia and/or ischemia of the extremities.
Antineoplastics | irinotecan | axitinib, dabrafenib, dasatinib, ibrutinib, nilotinib, sunitinib | bortezomib, busulphan, docetaxel, erlotinib, imatinib, ixabepilone, lapatinib, ponatinib, trimetrexate, vinca alkaloids | Irinotecan: The potential increase in plasma concentrations of irinotecan when coadministered with itraconazole may increase the risk of potentially fatal adverse events.
Antipsychotics, Anxiolytics and Hypnotics | lurasidone, oral midazolam, pimozide, triazolam |  | alprazolam, aripiprazole, buspirone, diazepam, haloperidol, midazolam IV, perospirone, quetiapine, ramelteon, risperidone | Midazolam, triazolam: Coadministration of itraconazole and oral midazolam, or triazolam may cause several-fold increases in plasma concentrations of these drugs. This may potentiate and prolong hypnotic and sedative effects, especially with repeated dosing or chronic administration of these agents.
 |  |  |  | Pimozide: The potential increase in plasma concentrations of pimozide when coadministered with itraconazole may increase the risk of serious cardiovascular events including QTc prolongation and torsade de pointes.
Antivirals |  | simeprevir | maraviroc, indinavir, ritonavir, saquinavir | Indinavir, ritonavir: See also under 'Drugs that may increase itraconazole plasma concentrations'.
Beta Blockers |  |  | nadolol
Calcium Channel Blockers | felodipine, nisoldipine |  | other dihydropyridines, verapamil | Calcium channel blockers can have a negative inotropic effect which may be additive to those of itraconazole. The potential increase in plasma concentrations of calcium channel blockers when co-administered with itraconazole may increase the risk of congestive heart failure.
 |  |  |  | Dihydropyridines: Concomitant administration of itraconazole may cause several-fold increases in plasma concentrations of dihydropyridines. Edema has been reported in patients concomitantly receiving itraconazole and dihydropyridine calcium channel blockers.
Cardiovascular Drugs, Miscellaneous | ranolazine | aliskiren, sildenafil, for the treatment of pulmonary hypertension | bosentan, riociguat | Ranolazine: The potential increase in plasma concentrations of ranolazine when coadministered with itraconazole may increase the risk of serious cardiovascular events including QTc prolongation.
Diuretics | eplerenone |  |  | Eplerenone: The potential increase in plasma concentrations of eplerenone when coadministered with itraconazole may increase the risk of hyperkalemia and hypotension.
Gastrointestinal Drugs | cisapride |  | aprepitant | Cisapride: The potential increase in plasma concentrations of cisapride when coadministered with itraconazole may increase the risk of serious cardiovascular events including QTc prolongation.
Immunosuppressants |  | everolimus, temsirolimus | budesonide, ciclesonide, cyclosporine, dexamethasone, fluticasone, methylprednisolone, rapamycin (also known as sirolimus), tacrolimus
Lipid Regulating Drugs | lovastatin, simvastatin |  | atorvastatin | The potential increase in plasma concentrations of atorvastatin, lovastatin, and simvastatin when coadministered with itraconazole may increase the risk of skeletal muscle toxicity, including rhabdomyolysis.
Respiratory Drugs |  | salmeterol
Urological Drugs | fesoterodine, in subjects with moderate to severe renal impairment, or moderate to severe hepatic impairment, solifenacin, in subjects with severe renal impairment or moderate to severe hepatic impairment | darifenacin, vardenafil | fesoterodine, oxybutynin, sildenafil, for the treatment of erectile dysfunction, solifenacin, tadalafil, tolterodine | Fesoterodine: The potential increase in plasma concentrations of the fesoterodine active metabolite may be greater in subjects with moderate to severe renal impairment, or moderate to severe hepatic impairment, which may lead to an increased risk of adverse reactions. Solifenacin: The potential increase in plasma concentrations of solifenacin in subjects with severe renal impairment or moderate to severe hepatic impairment, when coadministered with Itraconazole Capsules may increase the risk of serious cardiovascular events including QT prolongation.
Other | colchicine, in subjects with renal or hepatic impairment | colchicine, conivaptan, tolvaptan | cinacalcet | Colchicine: The potential increase in plasma concentrations of colchicine when coadministered with itraconazole may increase the risk of potentially fatal adverse events. Conivaptan and Tolvaptan: A safe and effective dose of either conivaptan or tolvaptan has not been established when coadministered with Itraconazole Capsules.

Drugs that may have their plasma concentrations decreased by itraconazole

Coadministration of itraconazole with the NSAID meloxicam may decrease the plasma concentration of meloxicam. It is recommended that meloxicam be used with caution when coadministered with itraconazole, and its effects or side effects be monitored. It is recommended that the dosage of meloxicam, if coadministered with itraconazole, be adjusted if necessary.

Pediatric Population

Interaction studies have only been performed in adults.

Carcinogenesis, Mutagenesis, and Impairment of Fertility

Itraconazole showed no evidence of carcinogenicity potential in mice treated orally for 23 months at dosage levels up to 80 mg/kg/day (approximately 10x the maximum recommended human dose [MRHD]). Male rats treated with 25 mg/kg/day (3.1× MRHD) had a slightly increased incidence of soft tissue sarcoma. These sarcomas may have been a consequence of hypercholesterolemia, which is a response of rats, but not dogs or humans, to chronic itraconazole administration. Female rats treated with 50 mg/kg/day (6.25× MRHD) had an increased incidence of squamous cell carcinoma of the lung (2/50) as compared to the untreated group. Although the occurrence of squamous cell carcinoma in the lung is extremely uncommon in untreated rats, the increase in this study was not statistically significant.

Itraconazole produced no mutagenic effects when assayed in DNA repair test (unscheduled DNA synthesis) in primary rat hepatocytes, in Ames tests with Salmonella typhimurium (6 strains) and Escherichia coli, in the mouse lymphoma gene mutation tests, in a sex-linked recessive lethal mutation (Drosophila melanogaster) test, in chromosome aberration tests in human lymphocytes, in a cell transformation test with C3H/10T½ C18 mouse embryo fibroblasts cells, in a dominant lethal mutation test in male and female mice, and in micronucleus tests in mice and rats.

Itraconazole did not affect the fertility of male or female rats treated orally with dosage levels of up to 40 mg/kg/day (5× MRHD), even though parental toxicity was present at this dosage level. More severe signs of parental toxicity, including death, were present in the next higher dosage level, 160 mg/kg/day (20× MRHD).

Pregnancy

Teratogenic effects

Pregnancy Category C

Itraconazole was found to cause a dose-related increase in maternal toxicity, embryotoxicity, and teratogenicity in rats at dosage levels of approximately 40–160 mg/kg/day (5–20× MRHD), and in mice at dosage levels of approximately 80 mg/kg/day (10× MRHD). Itraconazole has been shown to cross the placenta in a rat model. In rats, the teratogenicity consisted of major skeletal defects; in mice, it consisted of encephaloceles and/or macroglossia.

There are no studies in pregnant women. Itraconazole should be used for the treatment of systemic fungal infections in pregnancy only if the benefit outweighs the potential risk.

Itraconazole should not be administered for the treatment of onychomycosis to pregnant patients or to women contemplating pregnancy. Itraconazole should not be administered to women of childbearing potential for the treatment of onychomycosis unless they are using effective measures to prevent pregnancy and they begin therapy on the second or third day following the onset of menses. Effective contraception should be continued throughout itraconazole therapy and for 2 months following the end of treatment.

During post-marketing experience, cases of congenital abnormalities have been reported. (See ADVERSE REACTIONS: Post-marketing Experience.)

Nursing Mothers

Itraconazole is excreted in human milk; therefore, the expected benefits of itraconazole therapy for the mother should be weighed against the potential risk from exposure of itraconazole to the infant. The U.S. Public Health Service Centers for Disease Control and Prevention advises HIV-infected women not to breast-feed to avoid potential transmission of HIV to uninfected infants.

Pediatric Use

The efficacy and safety of itraconazole have not been established in pediatric patients.

The long-term effects of itraconazole on bone growth in children are unknown. In three toxicology studies using rats, itraconazole induced bone defects at dosage levels as low as 20 mg/kg/day (2.5× MRHD). The induced defects included reduced bone plate activity, thinning of the zona compacta of the large bones, and increased bone fragility. At a dosage level of 80 mg/kg/day (10× MRHD) over 1 year or 160 mg/kg/day (20× MRHD) for 6 months, itraconazole induced small tooth pulp with hypocellular appearance in some rats.

Geriatric Use

Clinical studies of Itraconazole Capsules did not include sufficient numbers of subjects aged 65 years and over to determine whether they respond differently from younger subjects. It is advised to use Itraconazole Capsules in these patients only if it is determined that the potential benefit outweighs the potential risks. In general, it is recommended that the dose selection for an elderly patient should be taken into consideration, reflecting the greater frequency of decreased hepatic, renal, or cardiac function, and of concomitant disease or other drug therapy.

Transient or permanent hearing loss has been reported in elderly patients receiving treatment with itraconazole. Several of these reports included concurrent administration of quinidine which is contraindicated (see BOXED WARNING: Drug Interactions, CONTRAINDICATIONS: Drug Interactions and PRECAUTIONS: Drug Interactions).

HIV-Infected Patients

Because hypochlorhydria has been reported in HIV-infected individuals, the absorption of itraconazole in these patients may be decreased.

Renal Impairment

Limited data are available on the use of oral itraconazole in patients with renal impairment. The exposure of itraconazole may be lower in some patients with renal impairment. Caution should be exercised when itraconazole is administered in this patient population and dose adjustment may be needed. (See CLINICAL PHARMACOLOGY: Special Populations and DOSAGE AND ADMINISTRATION.)

Hepatic Impairment

Limited data are available on the use of oral itraconazole in patients with hepatic impairment. Caution should be exercised when this drug is administered in this patient population. It is recommended that patients with impaired hepatic function be carefully monitored when taking itraconazole. It is recommended that the prolonged elimination half-life of itraconazole observed in the single oral dose clinical trial with Itraconazole Capsules in cirrhotic patients be considered when deciding to initiate therapy with other medications metabolized by CYP3A4.

In patients with elevated or abnormal liver enzymes or active liver disease, or who have experienced liver toxicity with other drugs, treatment with itraconazole is strongly discouraged unless there is a serious or life-threatening situation where the expected benefit exceeds the risk. It is recommended that liver function monitoring be done in patients with pre-existing hepatic function abnormalities or those who have experienced liver toxicity with other medications. (See CLINICAL PHARMACOLOGY: Special Populations and DOSAGE AND ADMINISTRATION.)

ADVERSE REACTIONS

Because clinical trials are conducted under widely varying conditions, adverse reaction rates observed in the clinical trials of a drug cannot be directly compared to rates in the clinical trials of another drug and may not reflect the rates observed in clinical practice.

Itraconazole has been associated with rare cases of serious hepatotoxicity, including liver failure and death. Some of these cases had neither pre-existing liver disease nor a serious underlying medical condition. If clinical signs or symptoms develop that are consistent with liver disease, treatment should be discontinued and liver function testing performed. The risks and benefits of itraconazole use should be reassessed. (See WARNINGS: Hepatic Effects and PRECAUTIONS: Hepatotoxicity and Information for Patients.)

Adverse Events in the Treatment of Systemic Fungal Infections

Adverse event data were derived from 602 patients treated for systemic fungal disease in U.S. clinical trials who were immunocompromised or receiving multiple concomitant medications. Treatment was discontinued in 10.5% of patients due to adverse events. The median duration before discontinuation of therapy was 81 days (range: 2 to 776 days). The table lists adverse events reported by at least 1% of patients.

Table 2: Clinical Trials of Systemic Fungal Infections: Adverse Events Occurring with an Incidence of Greater than or Equal to 1%
Body System/Adverse Event | Incidence (%) (N=602)
Gastrointestinal
Nausea | 11
Vomiting | 5
Diarrhea | 3
Abdominal Pain | 2
Anorexia | 1
Body as a Whole
Edema | 4
Fatigue | 3
Fever | 3
Malaise | 1
Skin and Appendages
Rash [Rash tends to occur more frequently in immunocompromised patients receiving immunosuppressive medications.] | 9
Pruritus | 3
Central/Peripheral Nervous System
Headache | 4
Dizziness | 2
Psychiatric
Libido Decreased | 1
Somnolence | 1
Cardiovascular
Hypertension | 3
Metabolic/Nutritional
Hypokalemia | 2
Urinary System
Albuminuria | 1
Liver and Biliary System
Hepatic Function Abnormal | 3
Reproductive System, Male
Impotence | 1

Adverse events infrequently reported in all studies included constipation, gastritis, depression, insomnia, tinnitus, menstrual disorder, adrenal insufficiency, gynecomastia, and male breast pain.

Adverse Events Reported in Toenail Onychomycosis Clinical Trials

Patients in these trials were on a continuous dosing regimen of 200 mg once daily for 12 consecutive weeks.

The following adverse events led to temporary or permanent discontinuation of therapy.

Table 3: Clinical Trials of Onychomycosis of the Toenail: Adverse Events Leading to Temporary or Permanent Discontinuation of Therapy
Adverse Event | Incidence (%) Itraconazole (N=112)
Elevated Liver Enzymes (greater than twice the upper limit of normal) | 4
Gastrointestinal Disorders | 4
Rash | 3
Hypertension | 2
Orthostatic Hypotension | 1
Headache | 1
Malaise | 1
Myalgia | 1
Vasculitis | 1
Vertigo | 1

The following adverse events occurred with an incidence of greater than or equal to 1% (N=112): headache: 10%; rhinitis: 9%; upper respiratory tract infection: 8%; sinusitis, injury: 7%; diarrhea, dyspepsia, flatulence, abdominal pain, dizziness, rash: 4%; cystitis, urinary tract infection, liver function abnormality, myalgia, nausea: 3%; appetite increased, constipation, gastritis, gastroenteritis, pharyngitis, asthenia, fever, pain, tremor, herpes zoster, abnormal dreaming: 2%.

Adverse Events Reported in Fingernail Onychomycosis Clinical Trials

Patients in these trials were on a pulse regimen consisting of two 1-week treatment periods of 200 mg twice daily, separated by a 3-week period without drug.

The following adverse events led to temporary or permanent discontinuation of therapy.

Table 4: Clinical Trials of Onychomycosis of the Fingernail: Adverse Events Leading to Temporary or Permanent Discontinuation of Therapy
Adverse Event | Incidence (%) Itraconazole (N=37)
Rash/Pruritus | 3
Hypertriglyceridemia | 3

The following adverse events occurred with an incidence of greater than or equal to 1% (N=37): headache: 8%; pruritus, nausea, rhinitis: 5%; rash, bursitis, anxiety, depression, constipation, abdominal pain, dyspepsia, ulcerative stomatitis, gingivitis, hypertriglyceridemia, sinusitis, fatigue, malaise, pain, injury: 3%.

Adverse Events Reported from Other Clinical Trials

In addition, the following adverse drug reaction was reported in patients who participated in Itraconazole Capsules clinical trials: Hepatobiliary Disorders: hyperbilirubinemia.

The following is a list of additional adverse drug reactions associated with itraconazole that have been reported in clinical trials of SPORANOX® (itraconazole) Oral Solution and itraconazole IV excluding the adverse reaction term "Injection site inflammation" which is specific to the injection route of administration:

Cardiac Disorders: cardiac failure, left ventricular failure, tachycardia;

General Disorders and Administration Site Conditions: face edema, chest pain, chills;

Hepatobiliary Disorders: hepatic failure, jaundice;

Investigations: alanine aminotransferase increased, aspartate aminotransferase increased, blood alkaline phosphatase increased, blood lactate dehydrogenase increased, blood urea increased, gamma-glutamyltransferase increased, urine analysis abnormal;

Metabolism and Nutrition Disorders: hyperglycemia, hyperkalemia, hypomagnesemia;

Psychiatric Disorders: confusional state;

Renal and Urinary Disorders: renal impairment;

Respiratory, Thoracic and Mediastinal Disorders: dysphonia, cough;

Skin and Subcutaneous Tissue Disorders: rash erythematous, hyperhidrosis;

Vascular Disorders: hypotension

Post-marketing Experience

Adverse drug reactions that have been first identified during post-marketing experience with itraconazole (all formulations) are listed in the table below. Because these reactions are reported voluntarily from a population of uncertain size, reliably estimating their frequency or establishing a causal relationship to drug exposure is not always possible.

Table 5: Postmarketing Reports of Adverse Drug Reactions
Blood and Lymphatic System Disorders: | Leukopenia, neutropenia, thrombocytopenia
Immune System Disorders: | Anaphylaxis; anaphylactic, anaphylactoid and allergic reactions; serum sickness; angioneurotic edema
Nervous System Disorders: | Peripheral neuropathy, paresthesia, hypoesthesia, tremor
Eye Disorders: | Visual disturbances, including vision blurred and diplopia
Ear and Labyrinth Disorders: | Transient or permanent hearing loss
Cardiac Disorders: | Congestive heart failure
Respiratory, Thoracic and Mediastinal Disorders: | Pulmonary edema, dyspnea
Gastrointestinal Disorders: | Pancreatitis, dysgeusia
Hepatobiliary Disorders: | Serious hepatotoxicity (including some cases of fatal acute liver failure), hepatitis
Skin and Subcutaneous Tissue Disorders: | Toxic epidermal necrolysis, Stevens-Johnson syndrome, acute generalized exanthematous pustulosis, erythema multiforme, exfoliative dermatitis, leukocytoclastic vasculitis, alopecia, photosensitivity, urticaria
Musculoskeletal and Connective Tissue Disorders: | Arthralgia
Renal and Urinary Disorders: | Urinary incontinence, pollakiuria
Reproductive System and Breast Disorders: | Erectile dysfunction
General Disorders and Administration Site Conditions: | Peripheral edema
Investigations: | Blood creatine phosphokinase increased

There is limited information on the use of itraconazole during pregnancy. Cases of congenital abnormalities including skeletal, genitourinary tract, cardiovascular and ophthalmic malformations as well as chromosomal and multiple malformations have been reported during post-marketing experience. A causal relationship with itraconazole has not been established. (See CLINICAL PHARMACOLOGY: Special Populations, CONTRAINDICATIONS, WARNINGS, and PRECAUTIONS: Drug Interactions for more information.)

OVERDOSAGE

Itraconazole is not removed by dialysis. In the event of accidental overdosage, supportive measures should be employed. Activated charcoal may be given if considered appropriate. In general, adverse events reported with overdose have been consistent with adverse drug reactions already listed in this package insert for itraconazole. (See ADVERSE REACTIONS.)

DOSAGE AND ADMINISTRATION

Itraconazole Capsules should be taken with a full meal to ensure maximal absorption. Itraconazole Capsules must be swallowed whole.

Itraconazole Capsules are a different preparation than SPORANOX® (itraconazole) Oral Solution and should not be used interchangeably.

Treatment of Blastomycosis and Histoplasmosis

The recommended dose is 200 mg once daily (2 capsules). If there is no obvious improvement, or there is evidence of progressive fungal disease, the dose should be increased in 100-mg increments to a maximum of 400 mg daily. Doses above 200 mg/day should be given in two divided doses.

Treatment of Aspergillosis

A daily dose of 200 to 400 mg is recommended.

Treatment in Life-Threatening Situations

In life-threatening situations, a loading dose should be used.

Although clinical studies did not provide for a loading dose, it is recommended, based on pharmacokinetic data, that a loading dose of 200 mg (2 capsules) three times daily (600 mg/day) be given for the first 3 days of treatment.

Treatment should be continued for a minimum of three months and until clinical parameters and laboratory tests indicate that the active fungal infection has subsided. An inadequate period of treatment may lead to recurrence of active infection.

Itraconazole Capsules and SPORANOX® (itraconazole) Oral Solution should not be used interchangeably. Only the oral solution has been demonstrated effective for oral and/or esophageal candidiasis.

Treatment of Onychomycosis

Toenails with or without fingernail involvement: The recommended dose is 200 mg (2 capsules) once daily for 12 consecutive weeks.

Treatment of Onychomycosis

Fingernails only: The recommended dosing regimen is 2 treatment pulses, each consisting of 200 mg (2 capsules) b.i.d. (400 mg/day) for 1 week. The pulses are separated by a 3-week period without itraconazole.

Use in Patients with Renal Impairment

Limited data are available on the use of oral itraconazole in patients with renal impairment. Caution should be exercised when this drug is administered in this patient population. (See CLINICAL PHARMACOLOGY: Special Populations and PRECAUTIONS.)

Use in Patients with Hepatic Impairment

Limited data are available on the use of oral itraconazole in patients with hepatic impairment. Caution should be exercised when this drug is administered in this patient population. (See CLINICAL PHARMACOLOGY: Special Populations, WARNINGS, and PRECAUTIONS.)

HOW SUPPLIED

Product: 68151-2718

NDC: 68151-2718-0 1 CAPSULE in a PACKAGE

Revised May 2015

Product of Ireland

Capsule contents manufactured by:
Janssen Pharmaceutica. NV.
Olen, Belgium

Manufactured by:
JOLLC, Gurabo, Puerto Rico 00778

Manufactured for:
Patriot Pharmaceuticals, LLC
Horsham, PA 19044

PATIENT INFORMATION

Itraconazole Capsules 100 mg

This summary contains important information about Itraconazole. This information is for patients who have been prescribed Itraconazole to treat fungal nail infections. If your doctor prescribed Itraconazole for medical problems other than fungal nail infections, ask your doctor if there is any information in this summary that does not apply to you. Read this information carefully each time you start to use Itraconazole. This information does not take the place of discussion between you and your doctor. Only your doctor can decide if Itraconazole is the right treatment for you. If you do not understand some of this information or have any questions, talk with your doctor or pharmacist.

WHAT IS THE MOST IMPORTANT INFORMATION I SHOULD KNOW ABOUT ITRACONAZOLE?

Itraconazole is used to treat fungal nail infections. However, Itraconazole is not for everyone. Do not take Itraconazole for fungal nail infections if you have had heart failure, including congestive heart failure. You should not take Itraconazole if you are taking certain medicines that could lead to serious or life-threatening medical problems. (See "Who Should Not Take Itraconazole?" below.)

If you have had heart, lung, liver, kidney or other serious health problems, ask your doctor if it is safe for you to take Itraconazole.

WHAT HAPPENS IF I HAVE A FUNGAL NAIL INFECTION?

Anyone can have a fungal nail infection, but it is usually found in adults. When a fungus infects the tip or sides of a nail, the infected part of the nail may turn yellow or brown. If not treated, the fungus may spread under the nail towards the cuticle. If the fungus spreads, more of the nail may change color, may become thick or brittle, and the tip of the nail may become raised. In some patients, this can cause pain and discomfort.

WHAT IS ITRACONAZOLE?

Itraconazole is a prescription medicine used to treat fungal infections of the toenails and fingernails. It is also used to treat some types of fungal infections in other areas of your body. We do not know if Itraconazole works in children with fungal nail infections or if it is safe for children to take.

Itraconazole comes in the form of capsules and liquid (oral solution). The capsule and liquid forms work differently, so you should not use one in place of the other. This Patient Information discusses only the capsule form of Itraconazole. You will get these capsules in a medicine bottle or an Itraconazole DosingPak. The DosingPak contains 28 capsules for treatment of your fungal nail infection.

Itraconazole goes into your bloodstream and travels to the source of the infection underneath the nail so that it can fight the infection there. Improved nails may not be obvious for several months after the treatment period is finished because it usually takes about 6 months to grow a new fingernail and 12 months to grow a new toenail.

WHO SHOULD NOT TAKE ITRACONAZOLE?

Itraconazole is not for everyone. Your doctor will decide if Itraconazole is the right treatment for you. Some patients should not take Itraconazole because they may have certain health problems or may be taking certain medicines that could lead to serious or life-threatening medical problems.

Tell your doctor and pharmacist the name of all the prescription and non-prescription medicines you are taking, including dietary supplements and herbal remedies. Also tell your doctor about any other medical conditions you have had, especially heart, lung, liver or kidney conditions; or if you have cystic fibrosis, or have had an allergic reaction to itraconazole or any other antifungal medicines.

Never take Itraconazole if you:

- have had heart failure, including congestive heart failure.
- are taking any of the medicines listed below. Dangerous or even life-threatening side effects could result:
  - cisapride (such as Propulsid®)
  - colchicine (such as Colcrys™) [if you also have pre-existing kidney or liver impairment]
  - disopyramide (such as Norpace®)
  - dofetilide (such as Tikosyn™)
  - dronedarone (such as Multaq®)
  - eplerenone (such as Inspra®)
  - ergot alkaloids (such as Migranal®, Ergonovine, Cafergot®, Methergine®)
  - felodipine (such as Plendil®)
  - fesoterodine (such as Toviaz®) [if you also have pre-existing kidney or liver impairment]
  - irinotecan (such as Camptosar®)
  - lovastatin (such as Mevacor®, Advicor®, Altocor™)
  - lurasidone (such as Latuda®)
  - methadone (such as Dolophine®)
  - midazolam (such as Versed®)
  - nisoldipine (such as Sular®)
  - pimozide (such as Orap®)
  - quinidine (such as Cardioquin®, Quinaglute®, Quinidex®)
  - ranolazine (such as Ranexa®)
  - simvastatin (such as Zocor®)
  - solifenacin (such as Vesicare®) [if you also have pre-existing kidney or liver impairment]
  - telithromycin (such as Ketek®) [if you also have pre-existing kidney or liver impairment]
  - ticagrelor (such as Brilinta®)
  - triazolam (such as Halcion®)
- have ever had an allergic reaction to itraconazole.

Taking Itraconazole with certain other medicines may lead to serious or life-threatening medical problems. Tell your doctor and pharmacist the name of all the prescription and non-prescription medicines you are taking, including dietary supplements and herbal remedies. Your doctor will decide if Itraconazole is the right treatment for you.

WHAT SHOULD I KNOW ABOUT ITRACONAZOLE AND PREGNANCY OR BREAST FEEDING?

Never take Itraconazole if you have a fungal nail infection and are pregnant or planning to become pregnant within 2 months after you have finished your treatment.

If you are able to become pregnant, you should use effective birth control during Itraconazole treatment and for 2 months after finishing treatment. Ask your doctor about effective types of birth control.

If you are breast-feeding, talk with your doctor about whether you should take Itraconazole.

HOW SHOULD I TAKE ITRACONAZOLE?

Always take Itraconazole Capsules during or right after a full meal.

Your doctor will decide the right dose for you. Depending on your infection, you will take Itraconazole once a day for 12 weeks, or twice a day for 1 week in a "pulse" dosing schedule. You will receive either a bottle of capsules or a DosingPak. Do not skip any doses. Be sure to finish all your Itraconazole as prescribed by your doctor.

If you have ever had liver problems, your doctor should do a blood test to check your condition. If you haven't had liver problems, your doctor may recommend blood tests to check the condition of your liver because patients taking Itraconazole can develop liver problems.

Itraconazole can sometimes cause dizziness or blurred/double vision. If you have these symptoms, do not drive or use machines.

If you forget to take or miss doses of Itraconazole, ask your doctor what you should do with the missed doses.

THE ITRACONAZOLE DosingPak

If you use the DosingPak, you will take Itraconazole for 1 week and then take no Itraconazole for the next 3 weeks before repeating the 1-week treatment. This is called "pulse dosing." The Itraconazole DosingPak contains enough medicine for one "pulse" (1 week of treatment).

The Itraconazole DosingPak comes with special instructions. It contains 7 pouches-one for each day of treatment. Inside each pouch is a card containing 4 capsules. Looking at the back of the card, fold it back along the dashed line and peel away the backing so that you can remove 2 capsules.

- Take 2 capsules in the morning and 2 capsules in the evening. This means you will take 4 capsules a day for 7 days. At the end of 7 days, you will have taken all of the capsules in the DosingPak box.
- After you finish the DosingPak, do not take any Itraconazole for the next 3 weeks. Even though you are not taking any capsules during this time, Itraconazole keeps working inside your nails to help fight the fungal infection.
- You will need more than one "pulse" to treat your fungal nail infection. When your doctor prescribes another pulse treatment, be sure to get your refill before the end of week 4.

Itraconazole Pulse Dosing
Take 2 Itraconazole capsules twice a day for 1 week
 | Day 1 |  | Day 2 |  | Day 3 |  | Day 4 |  | Day 5 |  | Day 6 |  | Day 7
 | AM | PM | AM | PM | AM | PM | AM | PM | AM | PM | AM | PM | AM | PM
Week 1 | // | // | // | // | // | // | // | // | // | // | // | // | // | //
Week 2 | For the next 3 weeks, do not take any Itraconazole capsules. Remember to get a refill before the end of Week 4 when your doctor prescribes another DosingPak.
Week 3 | For the next 3 weeks, do not take any Itraconazole capsules. Remember to get a refill before the end of Week 4 when your doctor prescribes another DosingPak.
Week 4 | For the next 3 weeks, do not take any Itraconazole capsules. Remember to get a refill before the end of Week 4 when your doctor prescribes another DosingPak.

WHAT ARE THE POSSIBLE SIDE EFFECTS OF ITRACONAZOLE?

The most common side effects include: headache, and digestive system problems (such as nausea, and abdominal pain).

Stop Itraconazole and call your doctor or get medical assistance right away if you have a severe allergic reaction. Symptoms of an allergic reaction may include skin rash, itching, hives, shortness of breath or difficulty breathing, and/or swelling of the face. Very rarely, an oversensitivity to sunlight, a tingling sensation in the limbs or a severe skin disorder can occur. If any of these symptoms occur, stop taking Itraconazole and contact your doctor.

Stop Itraconazole and call your doctor right away if you develop shortness of breath; have unusual swelling of your feet, ankles or legs; suddenly gain weight; are unusually tired; cough up white or pink phlegm; have unusual fast heartbeats; or begin to wake up at night. In rare cases, patients taking Itraconazole could develop serious heart problems, and these could be warning signs of heart failure.

Stop Itraconazole and call your doctor right away if you become unusually tired; lose your appetite; or develop nausea, abdominal pain, or vomiting, a yellow color to your skin or eyes, or dark colored urine or pale stools (bowel movements). In rare cases, patients taking Itraconazole could develop serious liver problems and these could be warning signs.

Stop Itraconazole and call your doctor right away if you experience any hearing loss symptoms. In very rare cases, patients taking Itraconazole have reported temporary or permanent hearing loss.

Call your doctor right away if you develop tingling or numbness in your extremities (hands or feet), if your vision gets blurry or you see double, if you hear a ringing in your ears, if you lose the ability to control your urine or urinate much more than usual.

Additional possible side effects include upset stomach, vomiting, constipation, fever, inflammation of the pancreas, menstrual disorder, erectile dysfunction, dizziness, muscle pain, painful joints, unpleasant taste, or hair loss. These are not all the side effects of Itraconazole. Your doctor or pharmacist can give you a more complete list.

WHAT SHOULD I DO IF I TAKE AN OVERDOSE OF ITRACONAZOLE?

If you think you took too much Itraconazole, call your doctor or local poison control center, or go to the nearest hospital emergency room right away.

HOW SHOULD I STORE ITRACONAZOLE?

Keep all medicines, including Itraconazole, out of the reach of children.

Store Itraconazole Capsules and the DosingPak at room temperature in a dry place away from light.

GENERAL ADVICE ABOUT ITRACONAZOLE

Medicines are sometimes prescribed for conditions that are not mentioned in patient information leaflets. Do not use Itraconazole for a condition for which it was not prescribed. Do not give Itraconazole to other people, even if they have the same symptoms you have. It may harm them.

This leaflet summarizes the most important information about Itraconazole. If you would like more information, talk with your doctor. You can ask your doctor or pharmacist for information about Itraconazole that is written for health professionals or you can call 1-800-667-8570.

This patient information has been approved by the U.S. Food and Drug Administration.

Revised May 2015

Product of Ireland

Manufactured by:
JOLLC, Gurabo, Puerto Rico 00778

Manufactured for:
Patriot Pharmaceuticals, LLC
Horsham, PA 19044